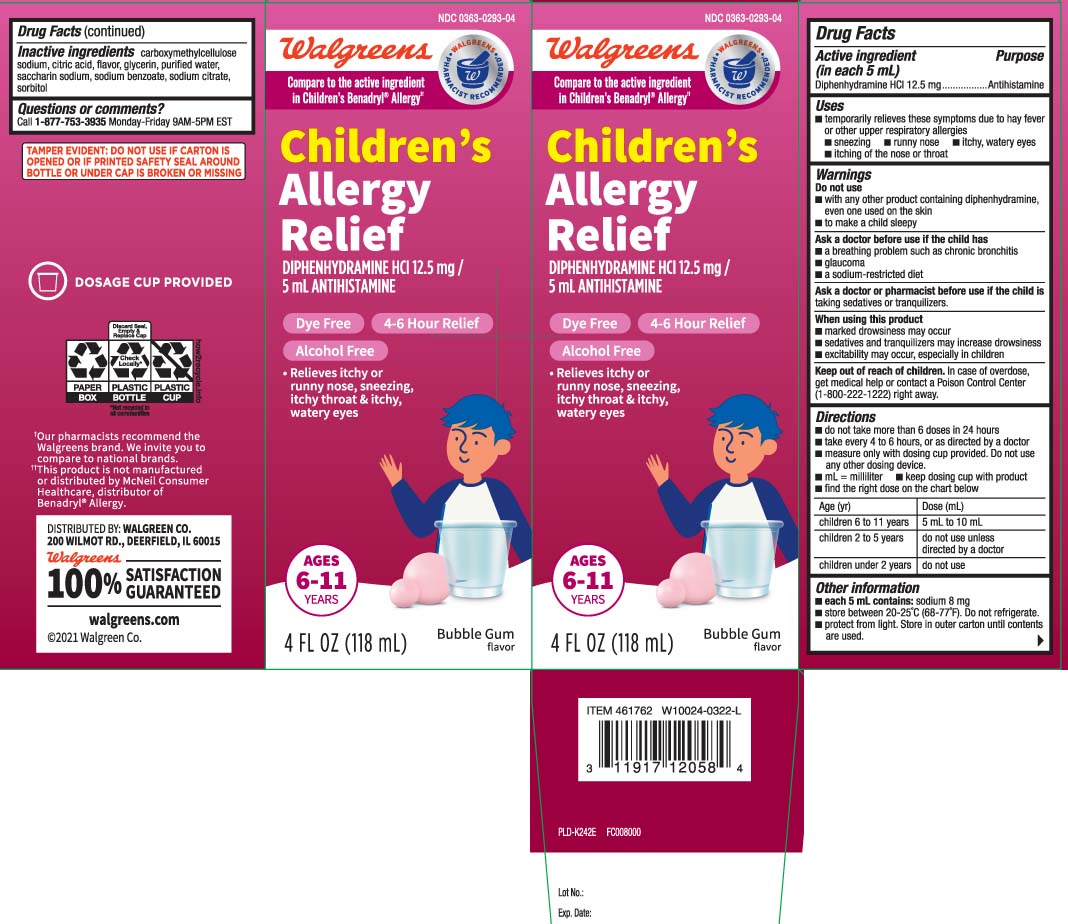 DRUG LABEL: Dye Free Wal Dryl Allergy
NDC: 0363-0293 | Form: LIQUID
Manufacturer: Walgreens
Category: otc | Type: HUMAN OTC DRUG LABEL
Date: 20250908

ACTIVE INGREDIENTS: DIPHENHYDRAMINE HYDROCHLORIDE 12.5 mg/5 mL
INACTIVE INGREDIENTS: ANHYDROUS CITRIC ACID; GLYCERIN; WATER; SODIUM BENZOATE; TRISODIUM CITRATE DIHYDRATE; CARBOXYMETHYLCELLULOSE SODIUM; SACCHARIN SODIUM; SORBITOL

Drug Facts

Active ingredient (in each 5 mL)

Diphenhydramine HCl 12.5 mg

Purpose

Antihistamine

Uses

temporarily relieves these symptoms due to hay fever or other upper respiratory allergies:

- sneezing
- runny nose
- itchy, watery eyes
- itching of the nose or throat

Warnings

Do not use

- with any other drug containing diphenhydramine, even one used on skin
- to make a child sleepy

Ask a doctor before use if the child has

- a breathing problem such as chronic bronchitis
- glaucoma
- a sodium-restricted diet

Ask a doctor or pharmacist before use if the child is

taking sedatives or tranquilizers

When using this product

- marked drowsiness may occur
- sedatives and tranquilizers may increase drowsiness
- excitability may occur, especially in children

Keep out of reach of children.

In case of overdose, get medical help or contact a Poison Control Center (1-800-222-1222) right away.

Directions

- do not take more than 6 doses in 24 hours
- take every 4 to 6 hours, or as directed by a doctor
- measure only with dosing cup provided. Do not use any other dosing device.
- mL = milliliter
- keep dosing cup with product
- find the right dose on the chart below

age (yr) | dose (mL)
children 6 to 11 years | 5 mL to 10 mL
children 2 to 5 years | do not use unless directed by a doctor
children under 2 years | do not use

Other information

- each 5 mL contains: sodium 8 mg
- store between 20-25°C (68-77°F). Do not refrigerate.
- Protect from light. Store in outer carton until contents are used.

Inactive ingredients

anhydrous citric acid, carboxymethycellulose sodium, flavor, glycerin, purified water, saccharin sodium, sodium benzoate, sodium citrate, sorbitol

Questions or comments?

Call 1-877-753-3935 Monday-Friday 9AM-5PM EST

Principal Display Panel

Compare to the active ingredient in Children's Benadryl® Allergy††

Children's

Allergy

DIPHENHYDRAMINE HCI 12.5 mg /

5 mL ANTIHISTAMINE

Dye Free 4-6 Hour Relief

Alcohol Free

- Relieves itchy or runny nose, sneezing, itchy throat & itchy, watery eyes

AGES

6-11 YEARS

Bubble Gum

DOSAGE CUP PROVIDED

FL OZ (mL)

††This product is not manufactured or distributed by McNeil Consumer Healthcare distributors of Benadryl® Allergy.

TAMPER EVIDENT: DO NOT USE IF CARTON IS OPENED OR IF PRINTED SAFETY SEAL AROUND BOTTLE OR UNDER CAP IS BROKEN OR MISSING.

DISTRIBUTED BY: WALGREEN CO.

200 WILMOT RD., DEERFIELD, IL 60015

walgreens.com

Package Label

WALGREENS Children's Allergy Relief Bubble Gum Flavor